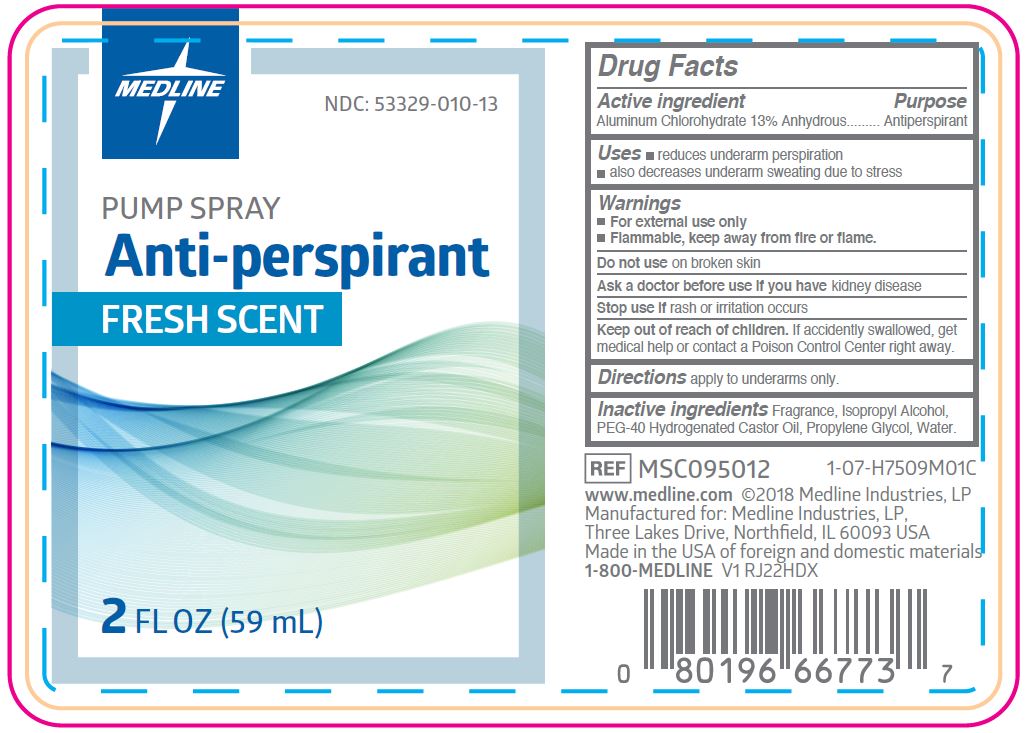 DRUG LABEL: Antiperspirant
NDC: 53329-010 | Form: SPRAY
Manufacturer: Medline Industries, LP
Category: otc | Type: HUMAN OTC DRUG LABEL
Date: 20260112

ACTIVE INGREDIENTS: ALUMINUM CHLOROHYDRATE 13 g/100 mL
INACTIVE INGREDIENTS: PEG-40 CASTOR OIL; ISOPROPYL ALCOHOL; PROPYLENE GLYCOL; WATER

010 Anti-perspirant

Active ingredient

Aluminum Chlorohydrate 13% w/v

Purpose

Antiperspirant

Uses

- reduces underarm perspiration
- also decreases underarm sweating due to stress

Warnings

For external use only.

Flammable, keep away from fire or flame.

Do not use

on broken skin

Ask a doctor before use if you have

kidney disease

Stop use if

rash or irritation occurs

Keep out of reach of children.

If accidentally swallowed, get medical help or contact a Poison Control Center right away.

Directions

apply to underarms only.

Inactive ingredients

fragrance, isopropyl alcohol, PEG-40 hydrogenated castor oil, propylene glycol, water

Manufacturing Information

Manufactured for: Medline Industries, LP

Three Lakes Drive, Northfield, IL 60093 USA

Made in USA with Foreign and Domestic Materials

www.medline.com

1-800-MEDLINE

REF: MSC095012

V1 RJ22HDX